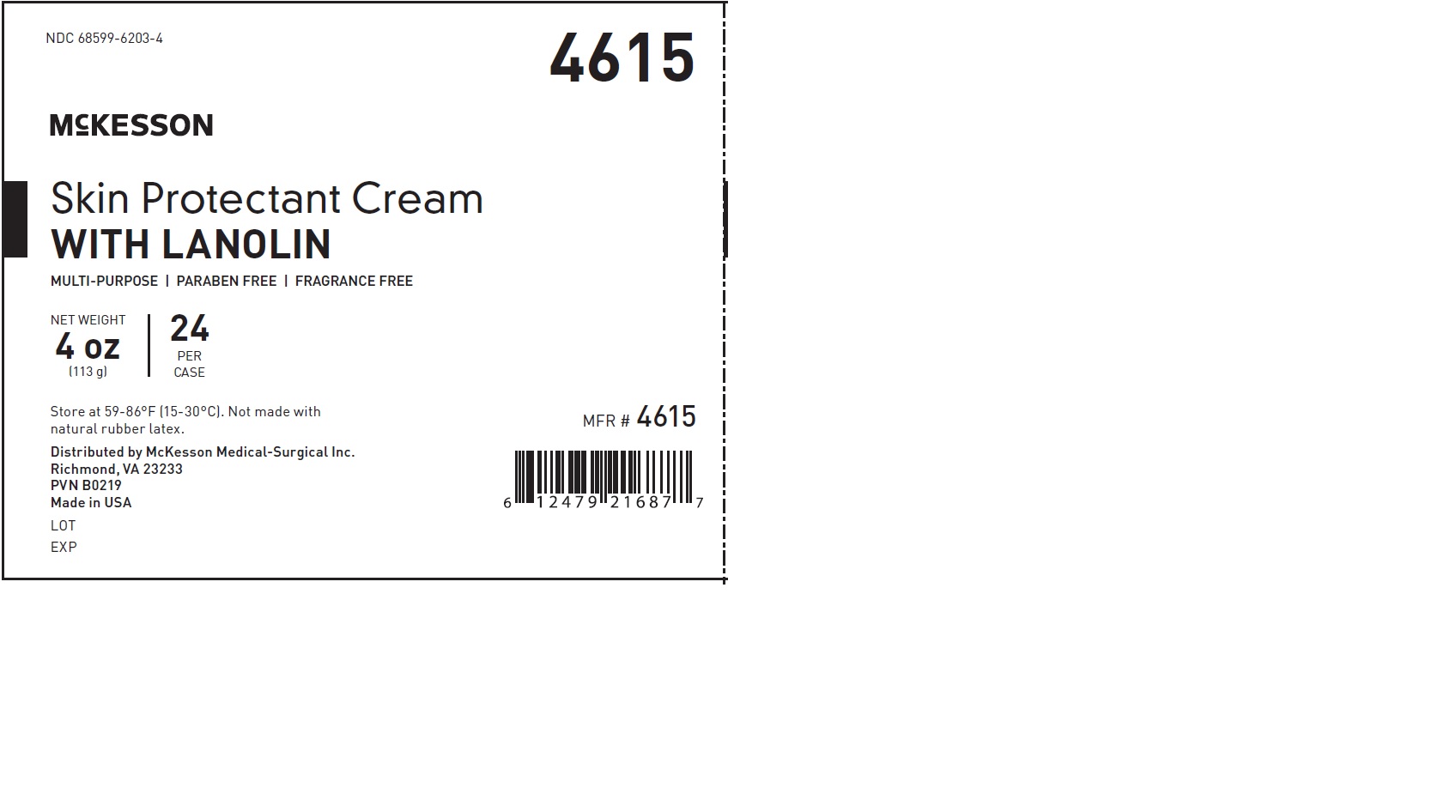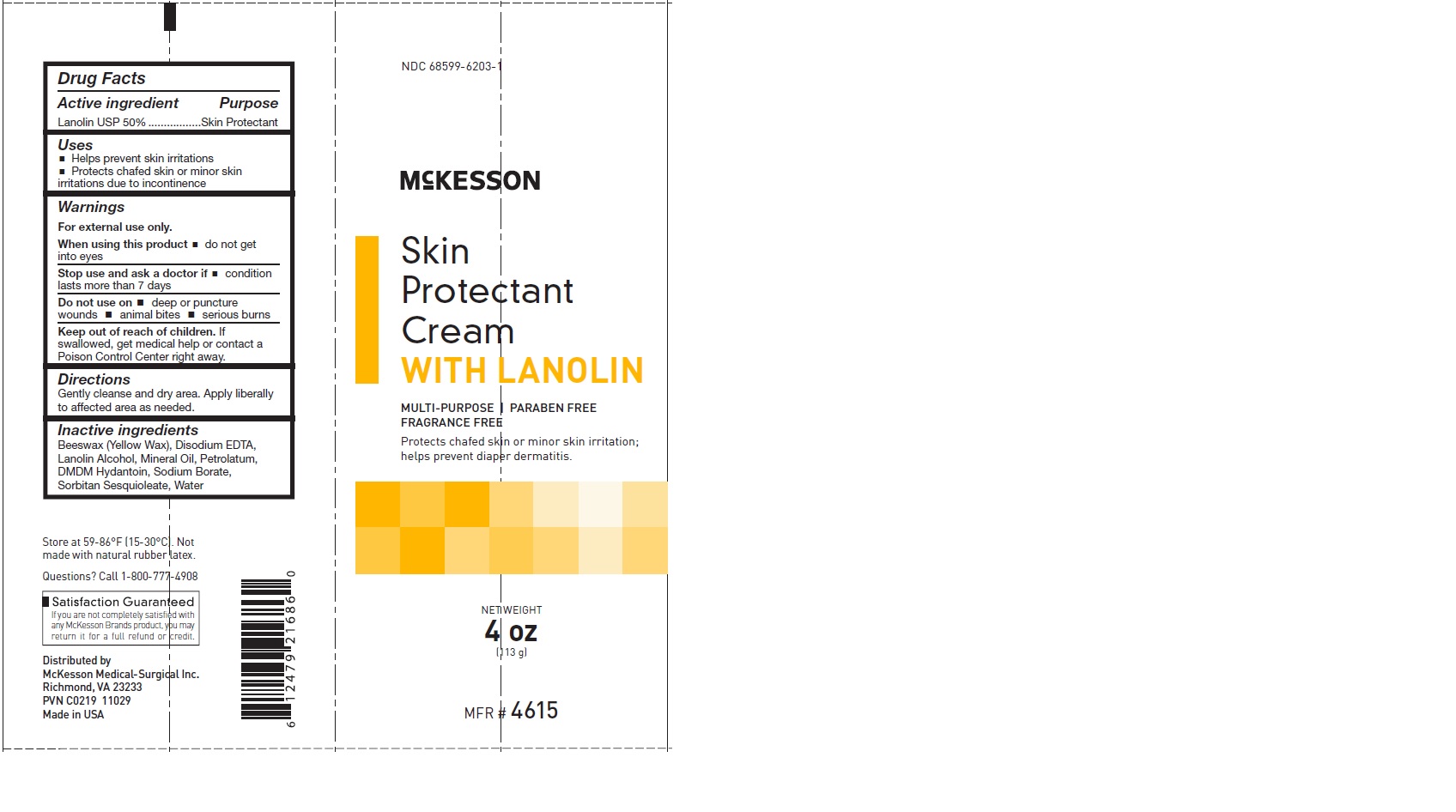 DRUG LABEL: Skin Protectant with Lanolin
NDC: 68599-6203 | Form: CREAM
Manufacturer: McKesson
Category: otc | Type: HUMAN OTC DRUG LABEL
Date: 20241014

ACTIVE INGREDIENTS: LANOLIN 50 g/100 g
INACTIVE INGREDIENTS: ALOE; SORBITAN SESQUIOLEATE; LANOLIN ALCOHOLS; DMDM HYDANTOIN; SODIUM BORATE; WATER; MINERAL OIL; YELLOW WAX; DISODIUM EDTA-COPPER

ACTIVE INGREDIENT

Lanolin 50%

Purpose: Skin protectant

Uses

- Helps prevent skin irritations
- Protects chafed skin or minor skin irritations due to incontinence

Warnings
For external use only.

When using this product

- do not get into eyes

Stop use and ask a doctor if

- condition lasts more than 7 days

Do not use on

- deep or puncture wounds
- animal bites
- serious burns

Keep out of reach of children. If swallowed, get medical help or contact a Poison Control Center right away.

Directions
Gently cleanse and dry area. Apply liberally to affected area as needed.

Inactive ingredients
Beeswax (Yellow Wax), Disodium EDTA, DMDM Hydantoin, Lanolin Alcohol, Mineral Oil, Petrolatum, Sodium Borate, Sorbitan Sesquioleate, Water

PACKAGE LABEL

NDC 68599-6203-1
McKesson

Skin Protectant Cream

WITH LANOLIN
MULTI-PURPOSE | PARABEN FREE
FRAGRANCE FREE

Protects chafed skin or minor skin irritation;
helps prevent diaper dermatitis.
NET Weight
4 oz
(133 g)
MFR # 4615